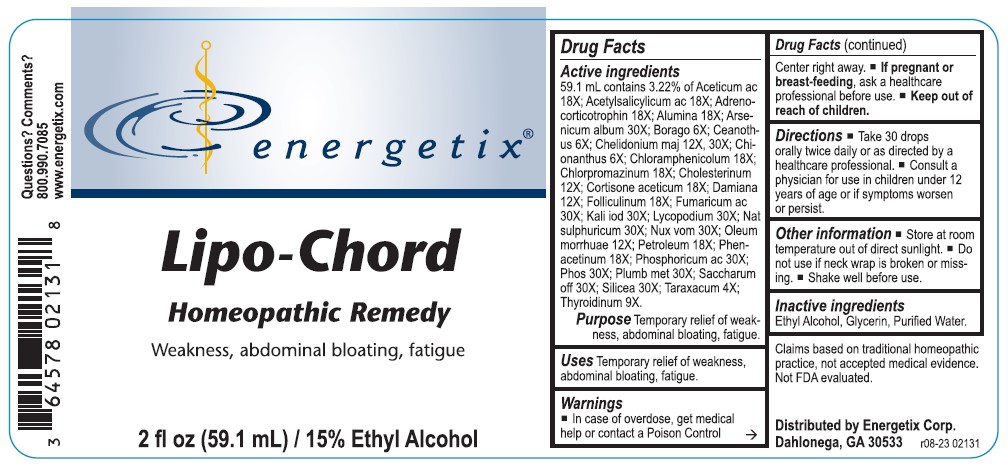 DRUG LABEL: Lipo-Chord
NDC: 64578-0145 | Form: LIQUID
Manufacturer: Energetix Corporation
Category: homeopathic | Type: HUMAN OTC DRUG LABEL
Date: 20241211

ACTIVE INGREDIENTS: ACETIC ACID 18 [hp_X]/59.1 mL; ASPIRIN 18 [hp_X]/59.1 mL; CORTICOTROPIN HUMAN 18 [hp_X]/59.1 mL; ALUMINUM OXIDE 18 [hp_X]/59.1 mL; ARSENIC TRIOXIDE 30 [hp_X]/59.1 mL; BORAGE 6 [hp_X]/59.1 mL; CEANOTHUS AMERICANUS LEAF 6 [hp_X]/59.1 mL; CHELIDONIUM MAJUS 12 [hp_X]/59.1 mL; CHIONANTHUS VIRGINICUS BARK 6 [hp_X]/59.1 mL; CHLORAMPHENICOL 18 [hp_X]/59.1 mL; CHLORPROMAZINE 18 [hp_X]/59.1 mL; CHOLESTEROL 12 [hp_X]/59.1 mL; CORTISONE ACETATE 18 [hp_X]/59.1 mL; TURNERA DIFFUSA LEAFY TWIG 12 [hp_X]/59.1 mL; ESTRONE 18 [hp_X]/59.1 mL; FUMARIC ACID 30 [hp_X]/59.1 mL; POTASSIUM IODIDE 30 [hp_X]/59.1 mL; LYCOPODIUM CLAVATUM SPORE 30 [hp_X]/59.1 mL; SODIUM SULFATE 30 [hp_X]/59.1 mL; STRYCHNOS NUX-VOMICA SEED 30 [hp_X]/59.1 mL; COD LIVER OIL 12 [hp_X]/59.1 mL; KEROSENE 18 [hp_X]/59.1 mL; PHENACETIN 18 [hp_X]/59.1 mL; PHOSPHORIC ACID 30 [hp_X]/59.1 mL; PHOSPHORUS 30 [hp_X]/59.1 mL; LEAD 30 [hp_X]/59.1 mL; SUCROSE 30 [hp_X]/59.1 mL; SILICON DIOXIDE 30 [hp_X]/59.1 mL; TARAXACUM OFFICINALE 4 [hp_X]/59.1 mL; THYROID, UNSPECIFIED 9 [hp_X]/59.1 mL
INACTIVE INGREDIENTS: WATER; GLYCERIN; ALCOHOL

Lipo-Chord

ACTIVE INGREDIENT

Active ingredients59. mL contains 3.22% of: Aceticum ac 18X; Acetylsalicylicum ac 18X; Adrenocorticotrophin 18X; Alumina 18X; Arsenicum album 30X; Borago 6X; Ceanothus 6X; Chelidonium maj 12X, 30X; Chionanthus 6X; Chloramphenicolum 18X; Chlorpromazinum 18X; Cholesterinum 12X; Cortisone aceticum 18X; Damiana 12X; Folliculinum 18X; Fumaricum ac 30X; Kali iod 30X; Lycopodium 30X; Nat sulphuricum 30X; Nux vom 30X; Oleum morrhuae 12X; Petroleum 18X; Phenacetinum 18X; Phosphoricum ac 30X; Phos 30X; Plumb met 30X; Saccharum off 30X; Silicea 30X; Taraxacum 4X; Thyroidinum 9X.

Claims based on traditional homeopathic practice, not accepted medical evidence. Not FDA evaluated.

Uses

Temporary relief of weakness, abdominal bloating, fatigue.

Warnings

- In case of overdose, get medical help or contact a Poison Control Center right away.
- If pregnant or breast-feeding, ask a healthcare professional before use.

- Keep out of reach of children.

Directions

- Take 30 drops orally twice daily or as directed by a healthcare professional.
- Consult a physician for use in children under 12 years of age or if symptoms worsen or persist.

Other information

- Store at room temperature out of direct sunlight.
- Do not use if neck wrap is broken or missing.
- Shake well before use.

Inactive ingredients

Ethyl Alcohol, Glycerin, Purified Water.

QUESTIONS

Distributed by Energetix Corp.

Dahlonega, GA 30533

Questions? Comments?

800.990.7085

www.energetix.com

PACKAGE LABEL

energetix

Lipo-Chord

Homeopathic Remedy

Weakness, abdominal bloating, fatigue

2 fl oz (59.1 mL) / 15% Ethyl Alcohol

Purpose Temporary relief of weakness, abdominal bloating, fatigue.